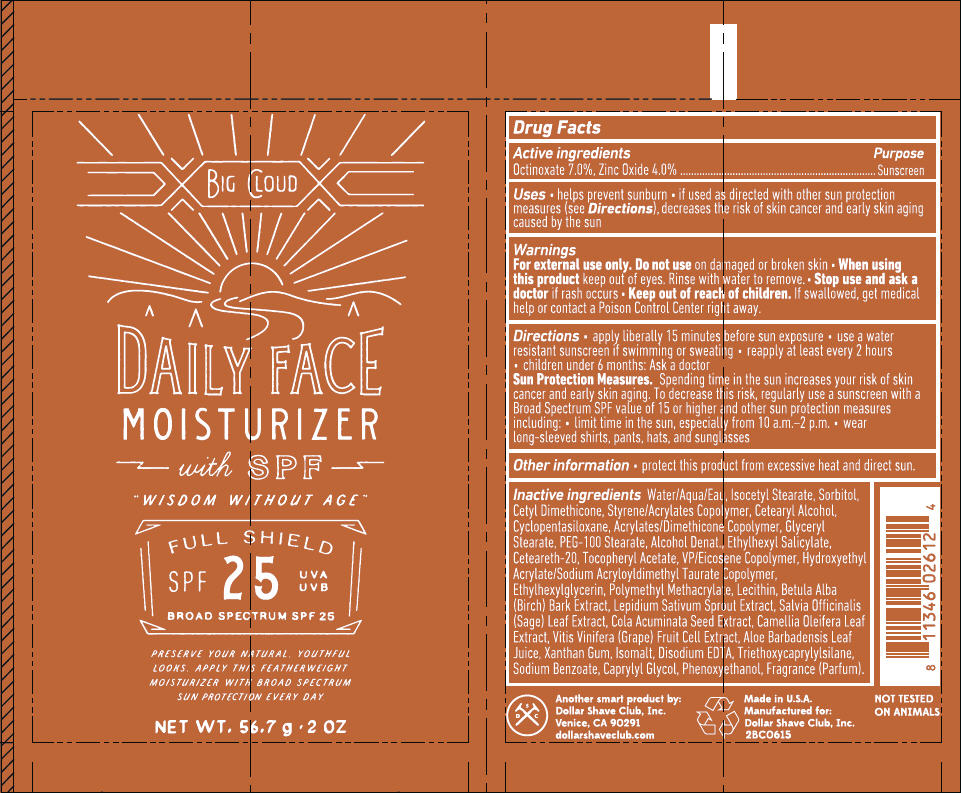 DRUG LABEL: Dollar Shave Club Daily Face Moisturizer Broad Spectrum SPF 25
NDC: 69522-2612 | Form: CREAM
Manufacturer: DOLLAR SHAVE CLUB, INC.
Category: otc | Type: HUMAN OTC DRUG LABEL
Date: 20171116

ACTIVE INGREDIENTS: OCTINOXATE 70 mg/1 g; ZINC OXIDE 40 mg/1 g
INACTIVE INGREDIENTS: WATER; ISOCETYL STEARATE; SORBITOL; Cetostearyl Alcohol; Cyclomethicone 5; Glyceryl Monostearate; PEG-100 Stearate; Alcohol; Octisalate; Polyoxyl 20 Cetostearyl Ether; .Alpha.-Tocopherol Acetate; Vinylpyrrolidone/Eicosene Copolymer; Hydroxyethyl Acrylate/Sodium Acryloyldimethyl Taurate Copolymer (100000 MPA.S AT 1.5%); Ethylhexylglycerin; Betula Pubescens Bark; Garden Cress Sprout; Sage; Cola Acuminata Seed; Camellia Oleifera Leaf; Aloe Vera Leaf; Xanthan Gum; Isomalt; Edetate Disodium Anhydrous; Triethoxycaprylylsilane; Sodium Benzoate; Caprylyl Glycol; Phenoxyethanol

Daily Face Moisturizer

Drug Facts

Active ingredients

Octinoxate 7.0%, Zinc Oxide 4.0%

Purpose

Sunscreen

Uses

- helps prevent sunburn
- if used as directed with other sun protection measures (see Directions), decreases the risk of skin cancer and early skin aging caused by the sun

Warnings

For external use only. Do not use on damaged or broken skin

- When using this product keep out of eyes. Rinse with water to remove.

- Stop use and ask a doctor if rash occurs

- Keep out of reach of children. If swallowed, get medical help or contact a Poison Control Center right away.

Directions

- apply liberally 15 minutes before sun exposure
- use a water resistant sunscreen if swimming or sweating
- reapply at least every 2 hours
- children under 6 months: Ask a doctor

Sun Protection Measures

Spending time in the sun increases your risk of skin cancer and early skin aging. To decrease this risk, regularly use a sunscreen with a Broad Spectrum SPF value of 15 or higher and other sun protection measures including:

- limit time in the sun, especially from 10 a.m.–2 p.m.
- wear long-sleeved shirts, pants, hats, and sunglasses

Other information

- protect this product from excessive heat and direct sun.

Inactive ingredients

Water/Aqua/Eau, Isocetyl Stearate, Sorbitol, Cetyl Dimethicone, Styrene/Acrylates Copolymer, Cetearyl Alcohol, Cyclopentasiloxane, Acrylates/Dimethicone Copolymer, Glyceryl Stearate, PEG-100 Stearate, Alcohol Denat., Ethylhexyl Salicylate, Ceteareth-20, Tocopheryl Acetate, VP/Eicosene Copolymer, Hydroxyethyl Acrylate/Sodium Acryloyldimethyl Taurate Copolymer, Ethylhexylglycerin, Polymethyl Methacrylate, Lecithin, Betula Alba (Birch) Bark Extract, Lepidium Sativum Sprout Extract, Salvia Officinalis (Sage) Leaf Extract, Cola Acuminata Seed Extract, Camellia Oleifera Leaf Extract, Vitis Vinifera (Grape) Fruit Cell Extract, Aloe Barbadensis Leaf Juice, Xanthan Gum, Isomalt, Disodium EDTA, Triethoxycaprylylsilane, Sodium Benzoate, Caprylyl Glycol, Phenoxyethanol, Fragrance (Parfum).

PRINCIPAL DISPLAY PANEL - 56.7 g Tube Label

BIG CLOUD

DAILY FACE
MOISTURIZER
with SPF

"WISDOM WITHOUT AGE"

FULL SHIELD
SPF
25
UVA
UVB
BROAD SPECTRUM SPF 25

PRESERVE YOUR NATURAL, YOUTHFUL
LOOKS. APPLY THIS FEATHERWEIGHT
MOISTURIZER WITH BROAD SPECTRUM
SUN PROTECTION EVERY DAY.

NET WT. 56.7 g • 2 OZ